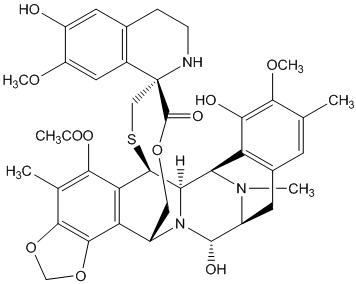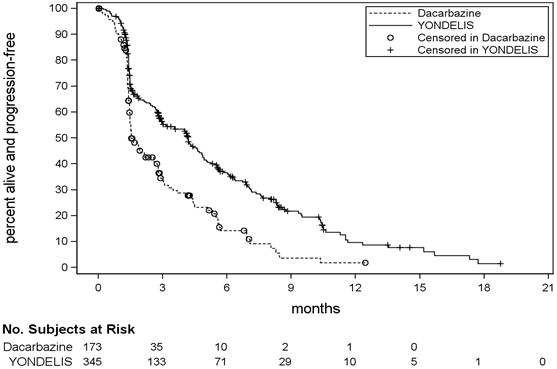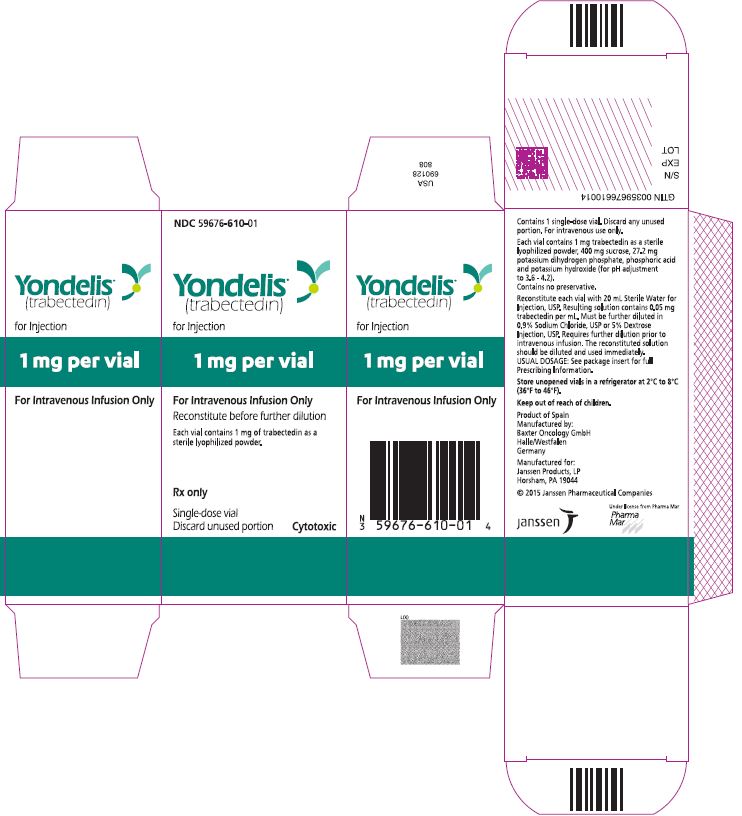 DRUG LABEL: YONDELIS
NDC: 59676-610 | Form: INJECTION, POWDER, LYOPHILIZED, FOR SOLUTION
Manufacturer: Janssen Products, LP
Category: prescription | Type: HUMAN PRESCRIPTION DRUG LABEL
Date: 20260106

ACTIVE INGREDIENTS: TRABECTEDIN 0.05 mg/1 mL
INACTIVE INGREDIENTS: SUCROSE; MONOBASIC POTASSIUM PHOSPHATE; PHOSPHORIC ACID; POTASSIUM HYDROXIDE

HIGHLIGHTS OF PRESCRIBING INFORMATION

These highlights do not include all the information needed to use YONDELIS safely and effectively. See full prescribing information for YONDELIS.
YONDELIS®(trabectedin) for injection, for intravenous use
Initial U.S. Approval: 2015

RECENT MAJOR CHANGES

Warnings and Precautions (5.7) | 12/2025

1 INDICATIONS AND USAGE

YONDELIS is an alkylating drug indicated for the treatment of adult patients with unresectable or metastatic liposarcoma or leiomyosarcoma who received a prior anthracycline-containing regimen (1)

2 DOSAGE AND ADMINISTRATION

- Administer at 1.5 mg/m^2as a 24-hour intravenous infusion, every 3 weeks through a central venous line (2.1, 2.6)
- Premedication: dexamethasone 20 mg intravenously, 30 min before each infusion (2.3)
- Hepatic Impairment: Administer at 0.9 mg/m^2as a 24-hour intravenous infusion, every 3 weeks through a central venous line in patients with moderate hepatic impairment (2.2)

3 DOSAGE FORMS AND STRENGTHS

For injection: 1 mg sterile lyophilized powder in a single-dose vial (3)

4 CONTRAINDICATIONS

Known hypersensitivity to trabectedin (4)

5 WARNINGS AND PRECAUTIONS

- Neutropenic sepsis: Severe, and fatal, neutropenic sepsis may occur. Monitor neutrophil count during treatment. Withhold YONDELIS for neutrophil count < 1,500/mcL (2.4, 5.1)
- Rhabdomyolysis: Rhabdomyolysis may occur. Monitor creatine phosphokinase (CPK) levels prior to each administration. Withhold YONDELIS for CPK more than 2.5 times the upper limit of normal. (2.4, 5.2)
- Hepatotoxicity: Hepatotoxicity may occur. Monitor and delay and/or reduce dose if needed (5.3)
- Cardiomyopathy: Severe and fatal cardiomyopathy can occur. Patients with left ventricular ejection fraction (LVEF) < lower limit of normal, prior cumulative anthracycline dose of ≥300 mg/m^2, age ≥65 years, or a history of cardiovascular disease may be at increased risk of developing new or worsening cardiac dysfunction. Discontinue YONDELIS in patients who develop decreased LVEF or cardiomyopathy (2.4, 5.4)
- Capillary leak syndrome: Monitor and discontinue YONDELIS for capillary leak syndrome (5.5)
- Embryo-fetal toxicity: Can cause fetal harm. Advise of potential risk to a fetus and use effective contraception (5.7, 8.1, 8.3)

6 ADVERSE REACTIONS

The most common (≥20%) adverse reactions are nausea, fatigue, vomiting, constipation, decreased appetite, diarrhea, peripheral edema, dyspnea, and headache. The most common (≥5%) grades 3–4 laboratory abnormalities are: neutropenia, increased ALT, thrombocytopenia, anemia, increased AST, and increased creatine phosphokinase. (6.1)

To report SUSPECTED ADVERSE REACTIONS, contact Janssen Products, LP at 1-800-526-7736 or FDA at 1-800-FDA-1088 or www.fda.gov/medwatch.

7 DRUG INTERACTIONS

- CYP3A inhibitors: Avoid concomitant strong CYP3A inhibitors (7.1)
- CYP3A inducers: Avoid concomitant strong CYP3A inducers (7.2)

8 USE IN SPECIFIC POPULATIONS

- Lactation: Advise not to breastfeed (8.2)
- Hepatic Impairment: Do not administer YONDELIS to patients with severe hepatic impairment (8.6, 12.3)

FULL PRESCRIBING INFORMATION

1 INDICATIONS AND USAGE

YONDELIS®is indicated for the treatment of adult patients with unresectable or metastatic liposarcoma or leiomyosarcoma who received a prior anthracycline-containing regimen [see Clinical Studies (14)] .

2 DOSAGE AND ADMINISTRATION

2.1 Recommended Dosage

The recommended dose is 1.5 mg/m^2administered as an intravenous infusion over 24 hours through a central venous line every 21 days (3 weeks), until disease progression or unacceptable toxicity.

2.2 Recommended Dosage in Patients with Hepatic Impairment

The recommended dosage of YONDELIS in patients with moderate hepatic impairment (bilirubin levels greater than 1.5 times to 3 times the upper limit of normal, and AST and ALT less than 8 times the upper limit of normal) is 0.9 mg/m^2every 21 days (3 weeks).

Do not administer YONDELIS to patients with severe hepatic impairment (bilirubin levels above 3 times the upper limit of normal, and any AST and ALT) [ see Use in Specific Populations (8.6)and Clinical Pharmacology (12.3)] .

2.3 Premedication

Administer dexamethasone 20 mg intravenously 30 minutes prior to each dose of YONDELIS.

2.4 Dosage Modifications for Adverse Reactions

Permanently discontinue YONDELIS for:

- Persistent adverse reactions requiring a delay in dosing of more than 3 weeks.
- Adverse reactions requiring dose reduction following YONDELIS administered at 1.0 mg/m^2for patients with normal hepatic function or at 0.3 mg/m^2for patients with pre-existing moderate hepatic impairment.
- Severe liver dysfunction: bilirubin two times the upper limit of normal, and AST or ALT three times the upper limit of normal, and alkaline phosphatase less than two times the upper limit of normal in the prior treatment cycle for patients with normal liver function at baseline.
- Exacerbation of liver dysfunction in patients with pre-existing moderate hepatic impairment.
- Capillary leak syndrome.
- Rhabdomyolysis.
- Grade 3 or 4 cardiac adverse events (AEs) indicative of cardiomyopathy or for subjects with an LVEF that decreases below the lower limit of normal.

The recommended dose modifications for adverse reactions are listed in Table 1. Once reduced, the dose of YONDELIS should not be increased in subsequent treatment cycles.

Table 1: Recommended Dosage Modification
Laboratory Result or Adverse Reaction | DELAY next dose of YONDELIS for up to 3 weeks | REDUCE next dose of YONDELIS by one dose level for adverse reaction(s) during prior cycle
Platelets | Less than 100,000 platelets/microliter | Less than 25,000 platelets/microliter
Absolute neutrophil count | Less than 1,500 neutrophils/microliter | - Less than 1,000 neutrophils/microliter with fever/infection - Less than 500 neutrophils/microliter lasting more than 5 days
Total bilirubin | Greater than the upper limit of normal | Greater than the upper limit of normal
Aspartate aminotransferase (AST) or alanine aminotransferase (ALT) | More than 2.5 times the upper limit of normal | More than 5 times the upper limit of normal
Alkaline phosphatase (ALP) | More than 2.5 times the upper limit of normal | More than 2.5 times the upper limit of normal
Creatine phosphokinase | More than 2.5 times the upper limit of normal | More than 5 times the upper limit of normal
Other non-hematologic adverse reactions | Grade 3 or 4 | Grade 3 or 4

The recommended starting doses and dose reductions for YONDELIS are listed in Table 2:

Table 2: Recommended Starting Doses and Dose Reductions
Starting Dose and Dose Reduction | For patients with normal hepatic function or mild hepatic impairment [Including patients with bilirubin greater than 1 to 1.5 times the upper limit of normal, and any AST or ALT.] prior to initiation of YONDELIS treatment | For patients with moderate hepatic impairment [Including patients with bilirubin levels greater than 1.5 times to 3 times the upper limit of normal, and AST and ALT less than 8 times the upper limit of normal.] prior to initiation of YONDELIS treatment
Starting Dose | 1.5 mg/m^2 | 0.9 mg/m^2
Dose Reduction
First dose reduction | 1.2 mg/m^2 | 0.6 mg/m^2
Second dose reduction | 1.0 mg/m^2 | 0.3 mg/m^2

2.5 Preparation for Administration

- YONDELIS is a hazardous drug. Follow applicable special handling and disposal procedures.^1
- Parenteral drug products should be inspected visually for particulate matter and discoloration prior to administration, whenever solution and container permit.
- Using aseptic technique, inject 20 mL of Sterile Water for Injection, USP into the vial. Shake the vial until complete dissolution. The reconstituted solution is clear, colorless to pale brownish-yellow, and contains 0.05 mg/mL of trabectedin.
- Inspect for particulate matter and discoloration prior to further dilution. Discard vial if particles or discoloration are observed.
- Immediately following reconstitution, withdraw the calculated volume of trabectedin and further dilute in 500 mL of 0.9% Sodium Chloride, USP or 5% Dextrose Injection, USP.
- Do not mix YONDELIS with other drugs.
- Discard any remaining solution within 30 hours of reconstituting the lyophilized powder.
- YONDELIS diluted solution is compatible with Type I colorless glass vials, polyvinylchloride (PVC) and polyethylene (PE) bags and tubing, PE and polypropylene (PP) mixture bags, polyethersulfone (PES) in-line filters, titanium, platinum or plastic ports, silicone and polyurethane catheters, and pumps having contact surfaces made of PVC, PE, or PE/PP.

2.6 Administration

- Infuse the reconstituted, diluted solution over 24 hours through a central venous line using an infusion set with a 0.2 micron polyethersulfone (PES) in-line filter.
- Complete infusion within 30 hours of initial reconstitution. Discard any unused portion of the reconstituted product or of the infusion solution.

3 DOSAGE FORMS AND STRENGTHS

For injection: 1 mg, lyophilized powder in single-dose vial for reconstitution.

4 CONTRAINDICATIONS

YONDELIS is contraindicated in patients with known severe hypersensitivity, including anaphylaxis, to trabectedin.

5 WARNINGS AND PRECAUTIONS

5.1 Neutropenic Sepsis

Neutropenic sepsis, including fatal cases, can occur with YONDELIS. In Trial ET743-SAR-3007, the incidence of Grade 3 or 4 neutropenia, based on laboratory values, in patients receiving YONDELIS was 43% (161/378). The median time to the first occurrence of Grade 3 or 4 neutropenia was 16 days (range: 8 days to 9.7 months); the median time to complete resolution of neutropenia was 13 days (range: 3 days to 2.3 months). Febrile neutropenia (fever ≥38.5 °C with Grade 3 or 4 neutropenia) occurred in 18 patients (5%) treated with YONDELIS. Ten patients (2.6%) experienced neutropenic sepsis, 5 of whom had febrile neutropenia, which was fatal in 4 patients (1.1%).

Assess neutrophil count prior to administration of each dose of YONDELIS and periodically throughout the treatment cycle. Withhold or reduce dose of YONDELIS based on severity of adverse reaction [see Dosage and Administration (2.4)] .

5.2 Rhabdomyolysis

YONDELIS can cause rhabdomyolysis and musculoskeletal toxicity. In Trial ET743-SAR-3007, rhabdomyolysis leading to death occurred in 3 (0.8%) of the 378 patients receiving YONDELIS. Elevations in creatine phosphokinase (CPK) occurred in 122 (32%) of the 378 patients receiving YONDELIS, including Grade 3 or 4 CPK elevation in 24 patients (6%), compared to 15 (9%) of the 172 patients receiving dacarbazine with any CPK elevation, including 1 patient (0.6%) with Grade 3 CPK elevation. Among the 24 patients receiving YONDELIS with Grade 3 or 4 CPK elevation, renal failure occurred in 11 patients (2.9%); rhabdomyolysis with the complication of renal failure occurred in 4 of these 11 patients (1.1%). The median time to first occurrence of Grade 3 or 4 CPK elevations was 2 months (range: 1 to 11.5 months). The median time to complete resolution was 14 days (range: 5 days to 1 month).

Assess CPK levels prior to each administration of YONDELIS. Withhold, reduce dose, or permanently discontinue based on severity of adverse reaction [see Dosage and Administration (2.4)] .

5.3 Hepatotoxicity

Hepatotoxicity, including hepatic failure, can occur with YONDELIS. Patients with serum bilirubin levels above the upper limit of normal or AST or ALT levels >2.5 × upper limit of normal were not enrolled in Trial ET743-SAR-3007. In Trial ET743-SAR-3007, the incidence of Grade 3–4 elevated liver function tests (LFTs; defined as elevations in ALT, AST, total bilirubin, or alkaline phosphatase) was 35% (134/378) in patients receiving YONDELIS. The median time to development of Grade 3–4 elevation in ALT or AST was 29 days (range: 3 days to 11.5 months). Of the 134 patients with Grade 3–4 elevations in LFTs, 114 (85%) experienced complete resolution with the median time to complete resolution of 13 days (range: 4 days to 4.4 months).

In Trial ET743-SAR-3007, the incidence of drug-induced liver injury (defined as concurrent elevation in ALT or AST of more than three times the upper limit of normal, alkaline phosphatase less than two times the upper limit of normal, and total bilirubin at least two times the upper limit of normal) was 1.3% (5/378) in patients receiving YONDELIS. ALT or AST elevation greater than eight times the upper limit of normal occurred in 18% (67/378) of patients receiving YONDELIS.

Assess LFTs prior to each administration of YONDELIS and as clinically indicated based on underlying severity of pre-existing hepatic impairment. Manage elevated LFTs with treatment interruption, dose reduction, or permanent discontinuation based on severity and duration of LFT abnormality [see Dosage and Administration (2.4)and Use in Specific Populations (8.6)].

5.4 Cardiomyopathy

Cardiomyopathy including cardiac failure, congestive heart failure, ejection fraction decreased, diastolic dysfunction, or right ventricular dysfunction can occur with YONDELIS. In Trial ET743-SAR-3007, a significant decrease in LVEF was defined as an absolute decrease of ≥15% or below the lower limit of normal with an absolute decrease of ≥5%. Patients with a history of New York Heart Association Class II to IV heart failure or abnormal left ventricular ejection fraction (LVEF) at baseline were ineligible. In Trial ET743-SAR-3007, cardiomyopathy occurred in 23 patients (6%) receiving YONDELIS and in four patients (2.3%) receiving dacarbazine. Grade 3 or 4 cardiomyopathy occurred in 15 patients (4%) receiving YONDELIS and 2 patients (1.2%) receiving dacarbazine; cardiomyopathy leading to death occurred in 1 patient (0.3%) receiving YONDELIS and in none of the patients receiving dacarbazine. The median time to development of Grade 3 or 4 cardiomyopathy in patients receiving YONDELIS was 5.3 months (range: 26 days to 15.3 months).

Patients with LVEF < lower limit of normal, prior cumulative anthracycline dose of ≥300 mg/m^2, age ≥65 years, or a history of cardiovascular disease may be at increased risk of cardiac dysfunction. Assess LVEF by echocardiogram (ECHO) or multigated acquisition (MUGA) scan before initiation of YONDELIS and at 2- to 3-month intervals thereafter until YONDELIS is discontinued. Discontinue treatment with YONDELIS based on severity of adverse reaction [see Dosage and Administration (2.4)] .

5.5 Capillary Leak Syndrome

Capillary leak syndrome (CLS) characterized by hypotension, edema, and hypoalbuminemia has been reported with YONDELIS, including serious CLS resulting in death. Monitor for signs and symptoms of CLS. Discontinue YONDELIS and promptly initiate standard management for patients with CLS, which may include a need for intensive care [see Adverse Reactions (6.2)] .

5.6 Extravasation Resulting in Tissue Necrosis

Extravasation of YONDELIS, resulting in tissue necrosis requiring debridement, can occur. Evidence of tissue necrosis can occur more than 1 week after the extravasation. There is no specific antidote for extravasation of YONDELIS. Administer YONDELIS through a central venous line [see Dosage and Administration (2.6)] .

5.7 Embryo-Fetal Toxicity

Based on its mechanism of action, YONDELIS can cause fetal harm when administered to a pregnant woman. Advise females of reproductive potential to use effective contraception during therapy and for at least 8 months after the last dose of YONDELIS. Advise males with female partners of reproductive potential to use effective contraception during therapy and for at least 5 months after the last dose of YONDELIS [see Use in Specific Populations (8.1, 8.3)] .

6 ADVERSE REACTIONS

The following adverse reactions are discussed in more detail in other sections of the labeling:

- Anaphylaxis [see Contraindications (4)]
- Neutropenic Sepsis [see Warnings and Precautions (5.1)]
- Rhabdomyolysis [see Warnings and Precautions (5.2)]
- Hepatotoxicity [see Warnings and Precautions (5.3)]
- Cardiomyopathy [see Warnings and Precautions (5.4)]
- Capillary Leak Syndrome [see Warnings and Precautions (5.5)]
- Extravasation Resulting in Tissue Necrosis [see Warnings and Precautions (5.6)]

6.1 Clinical Trials Experience

Because clinical trials are conducted under widely varying conditions, adverse reaction rates observed in the clinical trials of a drug cannot be directly compared to rates in the clinical trials of another drug and may not reflect the rates observed in practice.

The data described below reflect exposure to YONDELIS in 755 patients with soft tissue sarcoma including 197 (26%) patients exposed to YONDELIS for greater than or equal to 6 months and 57 (8%) patients exposed to YONDELIS for greater than or equal to 1 year. The safety of YONDELIS was evaluated in six open-label, single-arm trials, in which 377 patients received YONDELIS and one open-label, randomized, active-controlled clinical trial in which 378 patients received YONDELIS (Trial ET743-SAR-3007). All patients received YONDELIS at the recommended dosing regimen of 1.5 mg/m^2administered as an intravenous infusion over 24 hours once every 3 weeks (q3wk, 24-h). The median age was 54 years (range: 18 to 81 years), 63% were female, and all patients had metastatic soft tissue sarcoma.

Tables 3 and 4 present selected adverse reactions and laboratory abnormalities, respectively, observed in Trial ET743-SAR-3007, an open-label, randomized (2:1), active-controlled trial in which 550 patients with previously treated leiomyosarcoma or liposarcoma (dedifferentiated, myxoid round cell, or pleomorphic) received YONDELIS 1.5 mg/m^2intravenous infusion over 24 hours once every 3 weeks (n=378) or dacarbazine 1000 mg/m^2intravenous infusion over 20 to 120 minutes once every 3 weeks (n=172) [see Clinical Studies (14)] . All patients treated with YONDELIS were required to receive dexamethasone 20 mg intravenous injection 30 minutes prior to start of the YONDELIS infusion.

In Trial ET743-SAR-3007, patients had been previously treated with an anthracycline- and ifosfamide-containing regimen or with an anthracycline-containing regimen and one additional cytotoxic chemotherapy regimen. The trial excluded patients with known central nervous system metastasis, elevated serum bilirubin or significant chronic liver disease, such as cirrhosis or active hepatitis, and history of myocardial infarction within 6 months, history of New York Heart Association Class II to IV heart failure, or abnormal left ventricular ejection fraction at baseline. The median age of patients in Trial ET743-SAR-3007 was 57 years (range: 17 to 81 years), with 69% female, 77% White, 12% Black or African American, 4% Asian, and <1% American Indian or Alaska Native. The median duration of exposure to trabectedin was 13 weeks (range: 1 to 127 weeks) with 30% of patients exposed to YONDELIS for greater than 6 months and 7% of patients exposed to YONDELIS for greater than 1 year.

In Trial ET743-SAR-3007, adverse reactions resulting in permanent discontinuation of YONDELIS occurred in 26% (98/378) of patients; the most common were increased liver tests (defined as ALT, AST, alkaline phosphatase, bilirubin) (5.6%), thrombocytopenia (3.4%), fatigue (1.6%), increased creatine phosphokinase (1.1%), and decreased ejection fraction (1.1%). Adverse reactions that led to dose reductions occurred in 42% (158/378) of patients treated with YONDELIS; the most common were increased liver tests (24%), neutropenia (including febrile neutropenia) (8%), thrombocytopenia (4.2%), fatigue (3.7%), increased creatine phosphokinase (2.4%), nausea (1.1%), and vomiting (1.1%). Adverse reactions led to dose interruptions in 52% (198/378) of patients treated with YONDELIS; the most common were neutropenia (31%), thrombocytopenia (15%), increased liver tests (6%), fatigue (2.9%), anemia (2.6%), increased creatinine (1.1%), and nausea (1.1%).

The most common adverse reactions (≥20%) were nausea, fatigue, vomiting, constipation, decreased appetite, diarrhea, peripheral edema, dyspnea, and headache. The most common laboratory abnormalities (≥20%) were increases in AST or ALT, increased alkaline phosphatase, hypoalbuminemia, increased creatinine, increased creatine phosphokinase, anemia, neutropenia, and thrombocytopenia.

Table 3: Selected Adverse Reactions [Limited to adverse reactions at a rate of ≥10% in the trabectedin arm and at a rate higher in the trabectedin arm compared with dacarbazine arm by ≥5% in overall incidence or by ≥2% for Grade 3–4 adverse reactions.] Occurring in ≥10% of Patients Receiving YONDELIS and at a Higher Incidence than in the Control Arm - Trial ET743-SAR-3007
 | YONDELIS (N=378) |  | Dacarbazine (N=172)
System Organ Class Adverse Reaction | All Grades [Toxicity grade is based on NCI common toxicity criteria, version 4.0.] (%) | Grades 3–4 (%) | All Grades (%) | Grades 3–4 (%)
Gastrointestinal disorders
Nausea | 75 | 7 | 50 | 1.7
Vomiting | 46 | 6 | 22 | 1.2
Constipation | 37 | 0.8 | 31 | 0.6
Diarrhea | 35 | 1.6 | 23 | 0
General disorders and administration site conditions
Fatigue [Fatigue is a composite of the following adverse event terms: fatigue, asthenia, and malaise.] | 69 | 8 | 52 | 1.7
Peripheral edema | 28 | 0.8 | 13 | 0.6
Metabolism and nutrition disorders
Decreased appetite | 37 | 1.9 | 21 | 0.6
Respiratory, thoracic and mediastinal disorders
Dyspnea | 25 | 4.2 | 20 | 1.2
Nervous system disorders
Headache | 25 | 0.3 | 19 | 0
Musculoskeletal and connective tissue disorders
Arthralgia | 15 | 0 | 8 | 1.2
Myalgia | 12 | 0 | 6 | 0
Psychiatric disorders
Insomnia | 15 | 0.3 | 9 | 0

Other clinically important adverse reactions observed in <10% of patients (N=755) with soft tissue sarcoma receiving YONDELIS were:

Nervous system disorders: peripheral neuropathy, paresthesia, hypoesthesia.

Respiratory, thoracic, and mediastinal disorders: pulmonary embolism.

General disorders and administration site conditions: mucosal inflammation

Table 4: Incidence of Selected Treatment-Emergent Laboratory Abnormalities [Treatment-emergent laboratory abnormalities including those higher in the trabectedin arm compared with the dacarbazine arm by ≥5% (all Grades) or by ≥2% (Grade 3–4). Incidence based on number of patients who had both baseline and at least one on-study laboratory measurement.] - Trial ET743-SAR-3007
Laboratory Abnormalities | YONDELIS |  | Dacarbazine
Laboratory Abnormalities | All Grades (%) | Grades 3–4 (%) | All Grades (%) | Grades 3–4 (%)
Chemistry
Increased ALT | 90 | 31 | 33 | 0.6
Increased AST | 84 | 17 | 32 | 1.2
Increased alkaline phosphatase | 70 | 1.6 | 60 | 0.6
Hypoalbuminemia | 63 | 3.7 | 51 | 3.0
Increased creatinine | 46 | 4.2 | 29 | 1.2
Increased creatine phosphokinase | 33 | 6.4 | 9 | 0.6
Hyperbilirubinemia | 13 | 1.9 | 5 | 0.6
Hematology
Anemia | 96 | 19 | 79 | 12
Neutropenia | 66 | 43 | 47 | 26
Thrombocytopenia | 59 | 21 | 57 | 20
YONDELIS group (range: 373 to 377 patients) and dacarbazine group (range: 166 to 168 patients).

6.2 Postmarketing Experience

The following adverse reactions have been identified during post-approval use of YONDELIS. Because these reactions are reported voluntarily from a population of uncertain size, it is not always possible to reliably estimate their frequency or establish a causal relationship to drug exposure.

Vascular disorders: capillary leak syndrome

7 DRUG INTERACTIONS

7.1 Effect of Cytochrome CYP3A Inhibitors

Coadministration of YONDELIS with ketoconazole, a strong CYP3A inhibitor, increased systemic exposure of trabectedin by 66%. Avoid using strong CYP3A inhibitors (e.g., oral ketoconazole, itraconazole, posaconazole, voriconazole, clarithromycin, telithromycin, indinavir, lopinavir, ritonavir, boceprevir, nelfinavir, saquinavir, telaprevir, nefazodone, conivaptan) in patients taking YONDELIS. If a strong CYP3A inhibitor for short-term use (i.e., less than 14 days) must be used, administer the strong CYP3A inhibitor 1 week after the YONDELIS infusion, and discontinue it the day prior to the next YONDELIS infusion [see Clinical Pharmacology (12.3)] .

7.2 Effect of Cytochrome CYP3A Inducers

Coadministration of YONDELIS with rifampin, a strong CYP3A inducer, decreased systemic exposure of trabectedin by 31%. Avoid using strong CYP3A inducers (e.g., rifampin, phenobarbital, St. John's wort) in patients taking YONDELIS [see Clinical Pharmacology (12.3)] .

8 USE IN SPECIFIC POPULATIONS

8.1 Pregnancy

Risk Summary

Based on its mechanism of action, trabectedin can cause fetal harm when administered during pregnancy [see Clinical Pharmacology (12.1)] . There are no available data with the use of YONDELIS during pregnancy. Animal reproductive and developmental studies at relevant doses have not been conducted with trabectedin; however, placental transfer of trabectedin was demonstrated in pregnant rats. Advise pregnant woman of the potential risk to a fetus. The background risk of major birth defects and miscarriage for the indicated population are unknown; however, the background risk in the U.S. general population of major birth defects is 2 to 4% and of miscarriage is 15 to 20% of clinically recognized pregnancies.

8.2 Lactation

Risk Summary

There are no data on the presence of trabectedin in human milk, the effects on the breastfed child, or the effects on milk production. Because of the potential for serious adverse reactions from YONDELIS in a breastfed child, advise a nursing woman to discontinue nursing during treatment with and for 3 months after the last dose of YONDELIS.

8.3 Females and Males of Reproductive Potential

Pregnancy Testing

Verify the pregnancy status of females of reproductive potential prior to initiating YONDELIS [see Use in Specific Populations (8.1)] .

Contraception

Females

Advise female patients of reproductive potential to use effective contraception during and for 8 months after the last dose of YONDELIS [see Use in Specific Populations (8.1)] .

Males

YONDELIS may damage spermatozoa, resulting in possible genetic and fetal abnormalities. Advise males with a female sexual partner of reproductive potential to use effective contraception during and for 5 months after the last dose of YONDELIS [see Nonclinical Toxicology (13.1)] .

Infertility

YONDELIS may result in decreased fertility in males and females [see Nonclinical Toxicology (13.1)] .

8.4 Pediatric Use

Safety and effectiveness in pediatric patients have not been established.

Safety (n=61) and efficacy (n=58) were assessed across five open-label studies (NCT00006463, NCT01453283, NCT00005625, NCT00070109, and ET-B-023-00) in pediatric patients (aged 2 to <17 years) with pediatric histotypes of sarcoma (predominantly rhabdomyosarcoma, osteosarcoma, Ewing sarcoma, and non-rhabdomyosarcoma soft tissue sarcoma). No new safety signals were observed in pediatric patients across these studies.

Pharmacokinetic parameters in 17 pediatric patients (aged 3 to 17 years) were within the range of values previously observed in adults given the same dose per body surface area.

8.5 Geriatric Use

Clinical studies of YONDELIS did not include sufficient numbers of subjects aged 65 and over to determine whether they respond differently from younger subjects.

8.6 Hepatic Impairment

The mean trabectedin exposure was (97%) higher in patients with moderate (bilirubin levels greater than 1.5 to 3 times the upper limit of normal, and AST and ALT less than 8 times the upper limit of normal) hepatic impairment compared to patients with normal (total bilirubin ≤ the upper limit of normal, and AST and ALT ≤ the upper limit of normal) liver function. Reduce YONDELIS dose in patients with moderate hepatic impairment [see Dosage and Administration (2.2)and Clinical Pharmacology (12.3)] .

Do not administer YONDELIS to patients with severe hepatic impairment (bilirubin levels above 3 times the upper limit of normal, and any AST and ALT) [see Warnings and Precautions (5.3)] .

8.7 Renal Impairment

No dose adjustment is recommended in patients with mild [creatinine clearance (CLcr) 60–89 mL/min] or moderate (CLcr of 30–59 mL/min) renal impairment.

The pharmacokinetics of trabectedin has not been evaluated in patients with severe renal impairment (CLcr <30 mL/min) or end stage renal disease [see Clinical Pharmacology (12.3)] .

10 OVERDOSAGE

There is no specific antidote for YONDELIS. Hemodialysis is not expected to enhance the elimination of YONDELIS because trabectedin is highly bound to plasma proteins (97%) and not significantly renally excreted.

11 DESCRIPTION

Trabectedin is an alkylating drug with the chemical name (1' R,6 R,6a R,7 R,13 S,14 S,16 R)-5-(acetyloxy)-3',4',6,6a,7,13,14,16-octahydro-6',8,14-trihydroxy-7',9-dimethoxy-4,10,23-trimethyl-spiro[6,16-(epithiopropanoxymethano)-7,13-imino-12 H-1,3-dioxolo[7,8]isoquino[3,2- b][3]benzazocine-20,1'(2' H)-isoquinolin]-19-one. The molecular formula is C39H43N3O11S. The molecular weight is 761.84 daltons. The chemical structure is shown below:

Trabectedin is hydrophobic and has a low solubility in water.

YONDELIS®(trabectedin) for injection is supplied as a sterile lyophilized white to off-white powder/cake in a single-dose vial. Each single-dose vial contains 1 mg of trabectedin, 27.2 mg potassium dihydrogen phosphate, 400 mg sucrose, and phosphoric acid and potassium hydroxide (for pH adjustment to 3.6 – 4.2).

12 CLINICAL PHARMACOLOGY

12.1 Mechanism of Action

Trabectedin is an alkylating drug that binds guanine residues in the minor groove of DNA, forming adducts and resulting in a bending of the DNA helix towards the major groove. Adduct formation triggers a cascade of events that can affect the subsequent activity of DNA binding proteins, including some transcription factors, and DNA repair pathways, resulting in perturbation of the cell cycle and eventual cell death.

12.2 Pharmacodynamics

Cardiac Electrophysiology

The effect of trabectedin on the QT/QTc interval was evaluated in 75 patients who received placebo on day 1 and trabectedin (1.3 mg/m^2) as a 3-hour intravenous infusion on day 2. No patients in the study showed a QTc interval exceeding 500 msec or more than 60 msec increase from baseline, and no large changes in the mean QTc interval (i.e., >20 msec) were observed.

12.3 Pharmacokinetics

The pharmacokinetics of trabectedin is characterized by a rapid decline phase at the end of the infusion and slower exponential phases. Population pharmacokinetic analyses suggest that the pharmacokinetics of trabectedin is dose-proportional (over the dose range of 0.024 to 1.8 mg/m^2) and exposure is time-independent. No accumulation of trabectedin in plasma is observed upon repeated administrations every 3 weeks.

Distribution

Binding of trabectedin to human plasma proteins was approximately 97%, independent of trabectedin concentrations ranging from 10 ng/mL to 100 ng/mL. Steady state volume of distribution of trabectedin exceeds 5000 L.

Elimination

The estimated mean (% coefficient of variation) clearance of trabectedin is 31.5 L/hr (50%) and the terminal elimination half-life is approximately 175 hours.

Metabolism

CYP3A is the predominant CYP enzyme responsible for the hepatic metabolism of trabectedin.

Trabectedin was extensively metabolized with negligible unchanged drug in urine and feces following administration of trabectedin to humans.

Excretion

In patients with solid tumors, following a 3-hour or a 24-hour intravenous infusion of^14C-labeled trabectedin, 64% of the total administered radioactive dose was recovered in 24 days, with 58% in feces and 6% in urine.

Specific Populations

The following population characteristics are not associated with a clinically significant effect on the pharmacokinetics of trabectedin: sex, age (19 to 83 years), body weight (36 to 148 kg), body surface area (0.9 to 2.8 m^2), mild hepatic impairment, or mild to moderate renal impairment. The effects of severe hepatic impairment, severe renal impairment or end stage renal disease on trabectedin exposure are unknown.

Hepatic Impairment

The geometric mean dose normalized trabectedin exposure (AUC) increased by 97% (90% CI: 20%, 222%) in patients with moderate hepatic impairment (bilirubin levels greater than 1.5 times to 3 times the upper limit of normal and AST and ALT less than 8 times the upper limit of normal) following administration of a single YONDELIS dose of 0.58 mg/m^2or 0.9 mg/m^2compared to patients with normal liver function following administration of a single YONDELIS dose of 1.3 mg/m^2 [see Dosage and Administration (2.2)and Use in Specific Populations (8.6)] .

Drug Interactions

Effect of Strong CYP3A Inhibitors on Trabectedin

Coadministration of multiple doses of ketoconazole (200 mg twice daily for 7.5 days) with a single dose of YONDELIS (0.58 mg/m^2) on day 1 increased trabectedin dose-normalized AUC by 66% and Cmaxby 22% compared to a single YONDELIS dose (1.3 mg/m^2) given alone.

Effect of Strong CYP3A Inducers on Trabectedin

Coadministration of multiple doses of rifampin (600 mg daily for 6 days) with a single YONDELIS dose (1.3 mg/m^2) on day 6 decreased trabectedin AUC by 31% and Cmaxby 21% compared to a single YONDELIS dose (1.3 mg/m^2) given alone.

Effect of Trabectedin on CYP Enzymes

In vitro, trabectedin has limited inhibition or induction potential of major CYP enzymes (CYP1A2, 2A6, 2B6, 2C9, 2C19, 2D6, 2E1, and 3A4).

13 NONCLINICAL TOXICOLOGY

13.1 Carcinogenesis, Mutagenesis, Impairment of Fertility

Trabectedin is genotoxic in both in vitroand in vivostudies. Long-term carcinogenicity studies have not been performed.

Fertility studies with trabectedin were not performed. In male rats there were limited histopathological signs of hemorrhage and degeneration in the testes following repeated administration of trabectedin at doses approximately 0.2 times the 1.5 mg/m^2human dose based on body surface area.

14 CLINICAL STUDIES

The clinical efficacy and safety of YONDELIS in patients with metastatic or recurrent leiomyosarcoma or liposarcoma were demonstrated in Trial ET743-SAR-3007 (NCT01343277), a randomized (2:1), open-label, active-controlled trial comparing treatment with YONDELIS 1.5 mg/m^2as a 24-hour continuous intravenous infusion once every 3 weeks to dacarbazine 1000 mg/m^2intravenous infusion (20 to 120 minutes) once every 3 weeks. Treatment continued in both arms until disease progression or unacceptable toxicity; all patients in the YONDELIS arm were required to receive dexamethasone 20 mg intravenous injection prior to each YONDELIS infusion. Patients were required to have unresectable, locally advanced or metastatic leiomyosarcoma or liposarcoma (dedifferentiated, myxoid round cell, or pleomorphic) and previous treatment with an anthracycline- and ifosfamide-containing regimen or an anthracycline-containing regimen and one additional cytotoxic chemotherapy regimen. Randomization was stratified by subtype of soft tissue sarcoma (leiomyosarcoma vs. liposarcoma), ECOG performance status (0 vs. 1), and number of prior chemotherapy regimens (1 vs. ≥2). The efficacy outcome measures were investigator-assessed progression-free survival (PFS) according to the Response Evaluation Criteria in Solid Tumors (RECIST v1.1), overall survival (OS), objective response rate (ORR), and duration of response (DOR). Patients in the dacarbazine arm were not offered YONDELIS at the time of disease progression.

A total of 518 patients were randomized, 345 to the YONDELIS arm and 173 patients to the dacarbazine arm. The median patient age was 56 years (range: 17 to 81); 30% were male; 76% White, 12% Black, and 4% Asian; 73% had leiomyosarcomas and 27% liposarcomas; 49% had an ECOG PS of 0; and 89% received ≥2 prior chemotherapy regimens. The most common (≥20%) pre-study chemotherapeutic agents administered were doxorubicin (90%), gemcitabine (81%), docetaxel (74%), and ifosfamide (59%). Approximately 10% of patients had received pazopanib.

Trial ET743-SAR-3007 demonstrated a statistically significant improvement in PFS. An exploratory analysis of independent radiology committee-determined PFS, in a subgroup consisting of approximately 60% of the total population, provided similar results to the investigator-determined PFS. Efficacy results from Trial ET743-SAR-3007 are presented in the table below.

Table 5: Efficacy Results for Trial ET743-SAR-3007
Efficacy Endpoint | YONDELIS N=345 | Dacarbazine N=173
Progression-free survival
PFS Events, n (%) | 217 (63%) | 112 (65%)
Disease progression | 204 | 109
Death | 13 | 3
Median (95% CI) (months) | 4.2 (3.0, 4.8) | 1.5 (1.5, 2.6)
HR (95% CI) [Cox proportional hazards model with treatment group as the only covariate.] | 0.55 (0.44, 0.70)
p-value [Unstratified log rank test.] | <0.001
Overall survival [Based on 384 patients randomized to YONDELIS arm and 193 patients randomized to dacarbazine.]
Events, n (%) | 258 (67%) | 123 (64%)
Median (95% CI) (months) | 13.7 (12.2, 16.0) | 13.1 (9.1, 16.2)
HR (95% CI) | 0.93 (0.75, 1.15)
p-value | 0.49
Objective Response Rate (ORR: CR+PR)
Number of patients (%) | 23 (7%) | 10 (6%)
95% CI [Fisher's exact CI.] | (4.3, 9.8) | (2.8, 10.4)
Duration of Response (CR+ PR)
Median (95% CI) (months) | 6.9 (4.5, 7.6) | 4.2 (2.9, NE)
CR=Complete Response; PR=Partial Response; CI=Confidence Interval, HR=hazard ratio, NE=not estimable.

Figure 1: Kaplan-Meier Curves of Progression-Free Survival in Trial ET743-SAR-3007

15 REFERENCES

1. "OSHA Hazardous Drugs." OSHA.http://www.osha.gov/SLTC/hazardousdrugs/index.html

16 HOW SUPPLIED/STORAGE AND HANDLING

YONDELIS®is supplied in a single-dose glass vial containing 1 mg trabectedin. Each carton contains one vial (NDC: 59676-610-01).

Storage and Handling

Store YONDELIS vials in a refrigerator at 2 °C to 8 °C (36 °F to 46 °F).

YONDELIS is a hazardous drug. Follow applicable special handling and disposal procedures.^1

17 PATIENT COUNSELING INFORMATION

Advise the patient to read the FDA-approved patient labeling (Patient Information).

Myelosuppression: Inform patients of the risks of myelosuppression. Instruct patients to immediately contact their healthcare provider for fever or unusual bruising, bleeding, tiredness, or paleness [see Warnings and Precautions (5.1)] .

Rhabdomyolysis: Advise patients to contact their healthcare provider if they experience severe muscle pain or weakness, or if they experience reddish-brown urine [see Warnings and Precautions (5.2)] .

Hepatotoxicity: Advise patients to contact their healthcare provider immediately for yellowing of skin and eyes (jaundice), pain in the upper right quadrant, severe nausea or vomiting, difficulty in concentrating, disorientation, or confusion [see Warnings and Precautions (5.3)] .

Cardiomyopathy: Advise patients to contact their healthcare provider immediately for new onset chest pain, shortness of breath, fatigue, lower extremity edema, or heart palpitations [see Warnings and Precautions (5.4)] .

Capillary leak syndrome: Advise patients to report symptoms such as edema with or without hypotension [see Warnings and Precautions (5.5)and Adverse Reactions (6.2)] .

Extravasation: Inform patients of the risks of extravasation and to notify their healthcare provider for redness, swelling, itchiness and discomfort or leakage at the injection site [see Warnings and Precautions (5.6)] .

Hypersensitivity: Advise patients to seek immediate medical attention for symptoms of allergic reactions including difficulty breathing, chest tightness, wheezing, severe dizziness or light-headedness, swelling of the lips or skin rash [see Contraindications (4)] .

Embryofetal toxicity: Advise pregnant women of the potential risk to a fetus. Advise females to contact their healthcare provider if they become pregnant, or if pregnancy is suspected, during treatment with YONDELIS [see Warnings and Precautions (5.7)and Use in Specific Populations (8.1)] .

Females and males of reproductive potential: Advise females of reproductive potential to use effective contraception during treatment with YONDELIS and for at least 8 months after last dose. Advise males with female partners of reproductive potential to use effective contraception during treatment with YONDELIS and for at least 5 months after the last dose [see Warnings and Precautions (5.7)and Use in Specific Populations (8.3)] .

Lactation: Advise females not to breastfeed during treatment with and for 3 months after the last dose of YONDELIS [see Use in Specific Populations (8.2)] .

Manufactured for:
Janssen Products, LP
Horsham, PA 19044, USA

For patent information: www.janssenpatents.com

© Johnson & Johnson and its affiliates 2015

Under license from Pharma Mar, S.A.

PATIENT INFORMATION
YONDELIS®(yon-DEL-ess)
(trabectedin)
for injection, for intravenous use

What is YONDELIS?
YONDELIS is a prescription medicine used to treat adults with liposarcoma or leiomyosarcoma that:

- cannot be treated with surgery or has spread to other areas of the body (metastatic), and
- have received treatment with other cancer medicines, including medicines called anthracyclines.

It is not known if YONDELIS is safe and effective in children.

Who should not receive YONDELIS?
Do not receive YONDELIS if you have had a severe allergic reaction to trabectedin or any of the ingredients in YONDELIS. See the end of this leaflet for a complete list of ingredients in YONDELIS.

Before receiving YONDELIS, tell your healthcare provider about all of your medical conditions, including if you:

- have liver or kidney problems
- have or had a history of heart problems
- are pregnant or plan to become pregnant. YONDELIS can harm your unborn baby.
  Females who are able to become pregnant:
  - Your healthcare provider will do a pregnancy test before you start treatment with YONDELIS.
  - Tell your healthcare provider right away if you become pregnant or think you may be pregnant during treatment with YONDELIS.
  - Use an effective form of birth control (contraception) during treatment and for 8 months after your last dose of YONDELIS.
  Males with female partners who are able to become pregnant:
  - YONDELIS can damage sperm and may cause birth defects.
  - Use an effective form of birth control during your treatment and for 5 months after your last dose of YONDELIS.
- are breastfeeding or plan to breastfeed. It is not known if YONDELIS passes into your breast milk.

Do not breastfeed during treatment with and for 3 months after your last dose of YONDELIS.
Tell your healthcare provider about all the medicines you take, including prescription and over-the-counter medicines, vitamins, and herbal supplements. Using YONDELIS with certain other medicines may affect the way YONDELIS works and may increase your risk of side effects. Know the medicines you take and keep a list of them to show to your healthcare provider or pharmacist when you get a new medicine.

How will I receive YONDELIS?

- YONDELIS is given by an intravenous (IV) infusion into a vein over 24 hours. To help avoid irritation at the site where it is infused, YONDELIS is given to you into a large vein through a type of IV line called a central venous line.
- YONDELIS is usually given every 3 weeks.
- Before each treatment with YONDELIS, you will receive a steroid medicine to help reduce your risk of getting certain side effects.
- Your healthcare provider will decide how long you will continue treatment with YONDELIS.

What are the possible side effects of YONDELIS?
YONDELIS can cause serious side effects, including :

- Severe infections due to decreased white blood cells.Decreased or low white blood cell counts can lead to severe infection throughout the body (sepsis) and death. Tell your healthcare provider right away if you develop fever or other signs of infection.
- Muscle problems (rhabdomyolysis).YONDELIS can cause severe muscle problems and increased levels of an enzyme in your blood called creatine phosphokinase (CPK). Muscle problems can lead to death. Tell your healthcare provider right away if you develop severe muscle pain or weakness or if your urine changes to a reddish-brown color.
- Liver problems. Increased liver enzymes in your blood and severe liver problems, including liver failure, can happen. Tell your healthcare provider right away if you develop:

- yellowing of your skin and whites of your eyes
- pain in your upper right stomach-area (abdomen)
- nausea
- vomiting

- problems with concentration
- disorientation
- confusion

- Heart muscle problems.Heart muscle problems, including heart failure, can be severe and lead to death. Your healthcare provider will do a test to check your heart function before you start and during treatment with YONDELIS. Tell your healthcare provider right away if you develop new chest pain, shortness of breath, tiredness, swelling of your legs, ankles, or feet, or heart palpitations.
- Capillary leak syndrome (CLS).YONDELIS can cause fluid to leak from the blood vessels into the body’s tissues. CLS can cause symptoms that can lead to death. Tell your healthcare provider right away if you develop swelling, dizziness or lightheadedness with or without a sudden drop in blood pressure.
- Skin damage from leakage at or near the infusion site.YONDELIS can cause damage and death of tissue cells if it leaks into the tissues around your infusion site. You may need to have surgery to remove any dead tissue. Tell your healthcare provider right away if you see any YONDELIS leaking out of your vein or around the catheter during your infusion, or if you notice any redness, swelling, itching or discomfort at the infusion site at any time.
- Allergic reactions.Some people have had allergic reactions to YONDELIS, including severe reactions. Get emergency help right away if you develop any of the following signs or symptoms of an allergic reaction: difficulty breathing, chest tightness, wheezing, severe dizziness or lightheadedness, swelling of the lips, or skin rash.

The most common side effects of YONDELIS include:

- nausea
- tiredness
- vomiting
- constipation
- decreased appetite

- diarrhea
- swelling of your hands, ankles, or feet
- shortness of breath
- headache

The most common severe abnormal blood tests include:

- decreased white blood cell, platelet, and red blood cell (anemia) counts. Tell your healthcare provider right away if you develop fever or signs of infection, unusual bruising, bleeding, tiredness, or paleness.
- increased liver enzymes and CPK.

Your healthcare provider will do certain blood tests before you start YONDELIS and during treatment to check you for side effects, and to see how well you respond to the treatment.
Your healthcare provider may decrease or delay your dose if you develop serious side effects or may permanently stop treatment with YONDELIS if your side effects are severe.
YONDELIS may cause fertility problems in males and females, which may affect your ability to have children. Talk to your healthcare provider if this is a concern for you.
Tell your healthcare provider if you have any side effect that bothers you or that does not go away.
These are not all the possible side effects of YONDELIS. Call your doctor for medical advice about side effects. You may report side effects to FDA at 1-800-FDA-1088.

General information about the safe and effective use of YONDELIS
Medicines are sometimes prescribed for purposes other than those listed in a Patient Information leaflet. You can ask your healthcare provider or pharmacist for information about YONDELIS that is written for health professionals.

What are the ingredients in YONDELIS?
Active ingredient: trabectedin
Inactive ingredients:potassium dihydrogen phosphate, sucrose, phosphoric acid and potassium hydroxide.
Manufactured for: Janssen Products, LP, Horsham, PA 19044, USA
For more information, call 1-800-526-7736 or go to www.YONDELIS.com.
For patent information: www.janssenpatents.com

This Patient Information has been approved by the U.S. Food and Drug Administration.

Revised 12/2025

PRINCIPAL DISPLAY PANEL - 1 Vial Carton

NDC 59676-610-01

Yondelis®
(trabectedin)

for Injection

1 mg per vial

For Intravenous Infusion Only

Reconstitute before further dilution

Each vial contains 1 mg of trabectedin as a
sterile lyophilized powder.

Rx only

Single-dose vial
Discard any unused portion

Cytotoxic